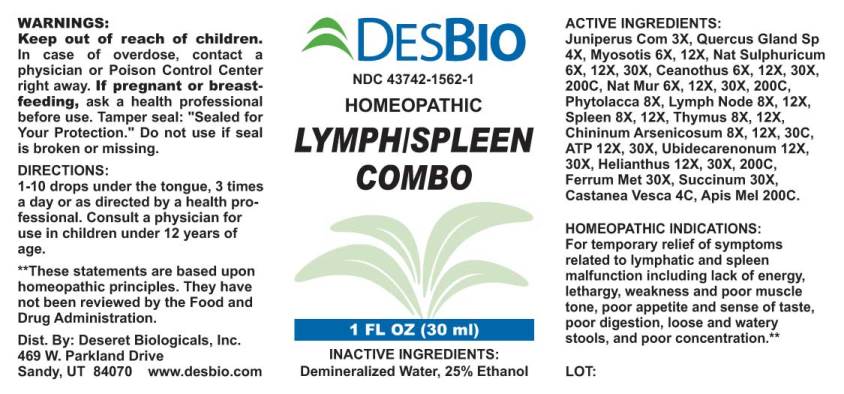 DRUG LABEL: Lymph/Spleen Combo
NDC: 43742-1562 | Form: LIQUID
Manufacturer: Deseret Biologicals, Inc.
Category: homeopathic | Type: HUMAN OTC DRUG LABEL
Date: 20240731

ACTIVE INGREDIENTS: JUNIPERUS COMMUNIS WHOLE 3 [hp_X]/1 mL; QUERCUS ROBUR NUT 4 [hp_X]/1 mL; MYOSOTIS ARVENSIS 6 [hp_X]/1 mL; SODIUM SULFATE 6 [hp_X]/1 mL; CEANOTHUS AMERICANUS LEAF 6 [hp_X]/1 mL; SODIUM CHLORIDE 6 [hp_X]/1 mL; PHYTOLACCA AMERICANA ROOT 8 [hp_X]/1 mL; SUS SCROFA LYMPH 8 [hp_X]/1 mL; SUS SCROFA SPLEEN 8 [hp_X]/1 mL; SUS SCROFA THYMUS 8 [hp_X]/1 mL; QUININE ARSENATE 8 [hp_X]/1 mL; ADENOSINE TRIPHOSPHATE DISODIUM 12 [hp_X]/1 mL; UBIDECARENONE 12 [hp_X]/1 mL; HELIANTHUS ANNUUS FLOWERING TOP 12 [hp_X]/1 mL; IRON 30 [hp_X]/1 mL; AMBER 30 [hp_X]/1 mL; CASTANEA SATIVA LEAF 4 [hp_C]/1 mL; APIS MELLIFERA 200 [hp_C]/1 mL
INACTIVE INGREDIENTS: WATER; ALCOHOL

Drug Facts:

ACTIVE INGREDIENTS:

Juniperus Communis 3X, Quercus Glandium Spiritus 4X, Myosotis Arvensis 6X, 12X, Natrum Sulphuricum 6X, 12X, Ceanothus Americanus 6X, 12X, 30X, 200C, Natrum Muriaticum 6X, 12X, 30X, 200C, Phytolacca Decandra 4X, Lymph Node (Suis) 8X, 12X, Spleen (Suis) 8X, 12X, Thymus (Suis) 8X, 12X, Chininum Arsenicosum 8X, 12X, 30C, Adenosinum Triphosphoricum Dinatrum 12X, 30X, Ubidecarenonum 12X, 30X, Helianthus Annuus 12X, 30X, 200C, Ferrum Metallicum 30X, Succinum 30X, Castanea Vesca 4C, Apis Mellifica 200C.

HOMEOPATHIC INDICATIONS:

For temporary relief of symptoms related to lymphatic and spleen malfunction including lack of energy, lethargy, weakness and poor muscle tone, poor appetite and sense of taste, poor digestion, loose and watery stools, and poor concentration.**

**These statements are based upon homeopathic principles. They have not been reviewed by the Food and Drug Administration.

WARNINGS:

Keep out of reach of children. In case of overdose, contact a physician or Poison Control Center right away.
If pregnant or breast-feeding, ask a health professional before use.
Tamper seal: "Sealed for Your Protection." Do not use if seal is broken or missing.

Keep out of reach of children. In case of overdose, contact a physician or Poison Control Center right away.

DIRECTIONS:

1-10 drops under the tongue, 3 times a day or as directed by a health professional. Consult a physician for use in children under 12 years of age.

HOMEOPATHIC INDICATIONS:

For temporary relief of symptoms related to lymphatic and spleen malfunction including lack of energy, lethargy, weakness and poor muscle tone, poor appetite and sense of taste, poor digestion, loose and watery stools, and poor concentration.**

**These statements are based upon homeopathic principles. They have not been reviewed by the Food and Drug Administration.

INACTIVE INGREDIENTS:

Demineralized Water, 25% Ethanol.

QUESTIONS:

Dist. By: Deseret Biologicals, Inc.
469 W. Parkland Drive
Sandy, UT 84070 www.desbio.com

PACKAGE LABEL DISPLAY:

DESBIO
NDC 43742-1562-1
HOMEOPATHIC
LYMPH/SPLEEN
COMBO
1 FL OZ (30 ml)